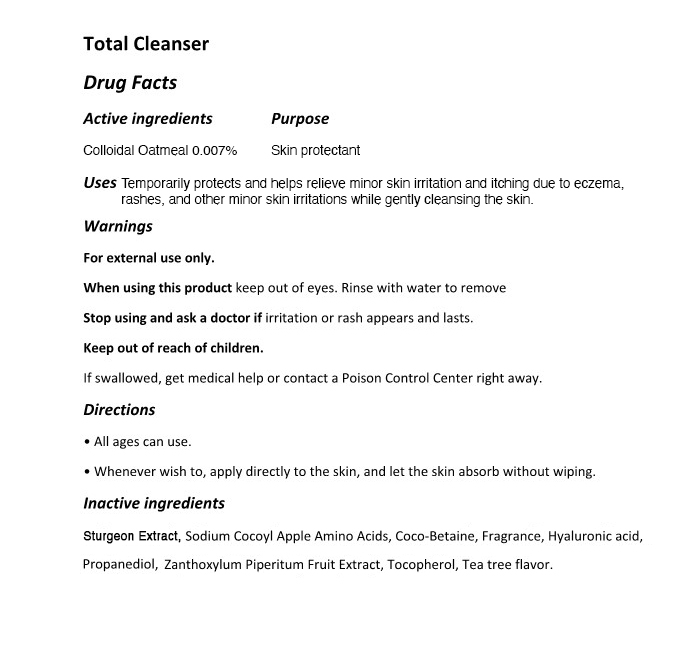 DRUG LABEL: The Zoeun Skin Total Cleanser
NDC: 83636-112 | Form: SOLUTION
Manufacturer: Sturgeonbio Co.,Ltd.
Category: otc | Type: HUMAN OTC DRUG LABEL
Date: 20251001

ACTIVE INGREDIENTS: OATMEAL 0.007 g/100 mL
INACTIVE INGREDIENTS: MELALEUCA ALTERNIFOLIA (TEA TREE) LEAF OIL; ZANTHOXYLUM PIPERITUM FRUIT PULP; COCAMIDOPROPYL BETAINE; FRAGRANCE 13576; PROPANEDIOL; HYALURONIC ACID; STURGEON, UNSPECIFIED; TOCOPHEROL; SODIUM COCOYL APPLE AMINO ACIDS

112 THE ZOEUN SKIN TOTAL CLEANSER

Active Ingredients

Colloidal Oatmeal 0.007%

Purpose

Skin protectant

Uses

Temporarily protects and helps relieve minor skin irritation and itching due to eczema, rashes, and other minor skin irritations while gently cleansing the skin.

Warnings

Keep out of reach of children.
If swallowed, get medical help or contact a Poison Control Center right away.

Warnings

Stop using and ask a doctor if irritation or rash appears and lasts.

Warnings

When using this product keep out of eyes. Rinse with water to remove

Warnings

For external use only.

Directions

• All ages can use.
• Whenever wish to, apply directly to the skin, and let the skin absorb without wiping.

Inactive Ingredients

Sturgeon Extract, Sodium Cocoyl Apple Amino Acids, Coco-Betaine, Fragrance, Hyaluronic acid, Propanediol, Zanthoxylum Piperitum Fruit Extract, Tocopherol, Tea tree flavor